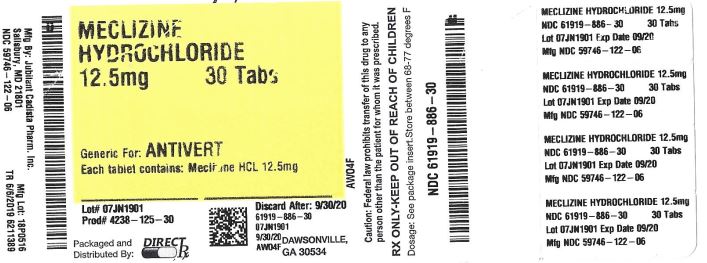 DRUG LABEL: MECLIZINE HYDROCHLORIDE
NDC: 61919-886 | Form: TABLET
Manufacturer: Direct_Rx
Category: prescription | Type: HUMAN PRESCRIPTION DRUG LABEL
Date: 20230112

ACTIVE INGREDIENTS: MECLIZINE HYDROCHLORIDE 12.5 mg/1 1
INACTIVE INGREDIENTS: MAGNESIUM STEARATE; CELLULOSE, MICROCRYSTALLINE; SILICON DIOXIDE; CROSCARMELLOSE SODIUM; LACTOSE MONOHYDRATE; FD&C BLUE NO. 1; ALUMINUM OXIDE

MECLIZINE HYDROCHLORIDE

DESCRIPTION

Meclizine HCl, USP an oral antiemetic, is a white or slightly yellowish, crystalline powder. It has the following structural formula:

[Structure of Meclizine HCl]

Chemically, Meclizine HCl is 1-(p-chloro-α-phenylbenzyl)-4-(m-methylbenzyl) piperazine dihydrochloride monohydrate.

Meclizine hydrochloride tablets, USP are available in two different strengths: 12.5 mg and 25 mg. In addition each tablet contains the following inactive ingredients: Colloidal Silicon Dioxide, Croscarmellose Sodium, Lactose Monohydrate, Magnesium Stearate, Microcrystalline Cellulose. Also, Meclizine hydrochloride tablets USP, 12.5 mg contains FD&C Blue #1 Aluminum Lake (11-13%) and Meclizine hydrochloride tablets USP, 25 mg contains D&C Yellow #10 Aluminum Lake (15-20%).

Each meclizine HCl 12.5 mg tablet contains 12.5 mg of meclizine dihydrochloride equivalent to 10.53 mg of meclizine free base.

Each meclizine HCl 25 mg tablet contains 25 mg of meclizine dihydrochloride equivalent to 21.07 mg of meclizine free base.

CLINICAL PHARMACOLOGY

Meclizine hydrochloride is an antihistamine that shows marked protective activity against nebulized histamine and lethal doses of intravenously injected histamine in guinea pigs. It has a marked effect in blocking the vasodepressor response to histamine, but only a slight blocking action against acetylcholine. Its activity is relatively weak in inhibiting the spasmogenic action of histamine on isolated guinea pig ileum.

Pharmacokinetics
The available pharmacokinetic information for meclizine following oral administration has been summarized from published literature.

Absorption
Meclizine is absorbed after oral administration with maximum plasma concentrations reaching at a median Tmax value of 3 hours post-dose (range: 1.5 to 6 hours) for the tablet dosage form.

Distribution
Drug distribution characteristics for meclizine in humans are unknown.

Metabolism
The metabolic fate of meclizine in humans is unknown. In an in vitro metabolic study using human hepatic microsome and recombinant CYP enzyme, CYP2D6 was found to be the dominant enzyme for metabolism of meclizine.

The genetic polymorphism of CYP2D6 that results in extensive-, poor-, intermediate- and ultra-rapid metabolizer phenotypes could contribute to large inter-individual variability in meclizine exposure.

Elimination
Meclizine has a plasma elimination half-life of about 5-6 hours in humans.

INDICATIONS AND USAGE

Meclizine hydrochloride tablets are indicated for the treatment of vertigo associated with diseases affecting the vestibular system.

CONTRAINDICATIONS

Meclizine hydrochloride tablets are contraindicated in individuals who have shown a previous hypersensitivity to it.

WARNINGS

Since drowsiness may, on occasion, occur with use of this drug, patients should be warned of this possibility and cautioned against driving a car or operating dangerous machinery.

Patients should avoid alcoholic beverages while taking this drug.

Due to its potential anticholinergic action, this drug should be used with caution in patients with asthma, glaucoma, or enlargement of the prostate gland.

PRECAUTIONS

Pediatric Use
Clinical studies establishing safety and effectiveness in children have not been done; therefore, usage is not recommended in children under 12 years of age.

Pregnancy
Teratogenic Effects. Pregnancy Category B.
Reproduction studies in rats have shown cleft palates at 25-50 times the human dose. Epidemiological studies in pregnant women, however, do not indicate that meclizine increases the risk of abnormalities when administered during pregnancy. Despite the animal findings, it would appear that the possibility of fetal harm is remote. Nevertheless, meclizine, or any other medication, should be used during pregnancy only if clearly necessary.

Nursing Mothers
It is not known whether this drug is excreted in human milk. Because many drugs are excreted in human milk, caution should be exercised when meclizine is administered to a nursing woman.

Hepatic Impairment
The effect of hepatic impairment on the pharmacokinetics of meclizine has not been evaluated. As meclizine undergoes metabolism, hepatic impairment may result in increased systemic exposure of the drug. Treatment with meclizine should be administered with caution in patients with hepatic impairment.

Renal Impairment
The effect of renal impairment on the pharmacokinetics of meclizine has not been evaluated. Due to a potential for drug/metabolite accumulation, meclizine should be administered with caution in patients with renal impairment and in the elderly as renal function generally declines with age.

Drug Interactions
There may be increased CNS depression when meclizine is administered concurrently with other CNS depressants, including alcohol, tranquilizers, and sedatives. (see WARNINGS).

Based on in-vitro evaluation, meclizine is metabolized by CYP2D6. Therefore there is a possibility for a drug interaction between meclizine and CYP2D6 inhibitors.

ADVERSE REACTIONS

Anaphylactoid reaction, drowsiness, dry mouth, headache, fatigue, vomiting and, on rare occasions, blurred vision have been reported.

To report SUSPECTED ADVERSE REACTIONS, contact Jubilant Cadista Pharmaceuticals Inc. at 1-800-313-4623 or FDA at 1-800-FDA-1088 or www.fda.gov/medwatch.

DOSAGE AND ADMINISTRATION

The recommended dose is 25 to 100 mg daily administered orally, in divided dosage, depending upon clinical response.

HOW SUPPLIED

Meclizine hydrochloride tablets, USP are available in the following strengths and package sizes:

12.5 mg (Blue, oval shaped tablets, debossed with “TL 122” with score on one side and plain on the other side.)
Bottles of 100
Bottles of 1000

25 mg (Yellow, oval shaped tablets, debossed with “TL 121” with score on one side and plain on the other side.)
Bottles of 100
Bottles of 1000

Store at 20 to 25°C (68 to 77°F) [See USP Controlled Room Temperature].

Dispense in a tight, light-resistant container (USP).

Keep this and all medication out of the reach of children.

Manufactured By:
Jubilant Cadista Pharmaceuticals Inc.
Salisbury, MD 21801, USA

Revised 01/2019